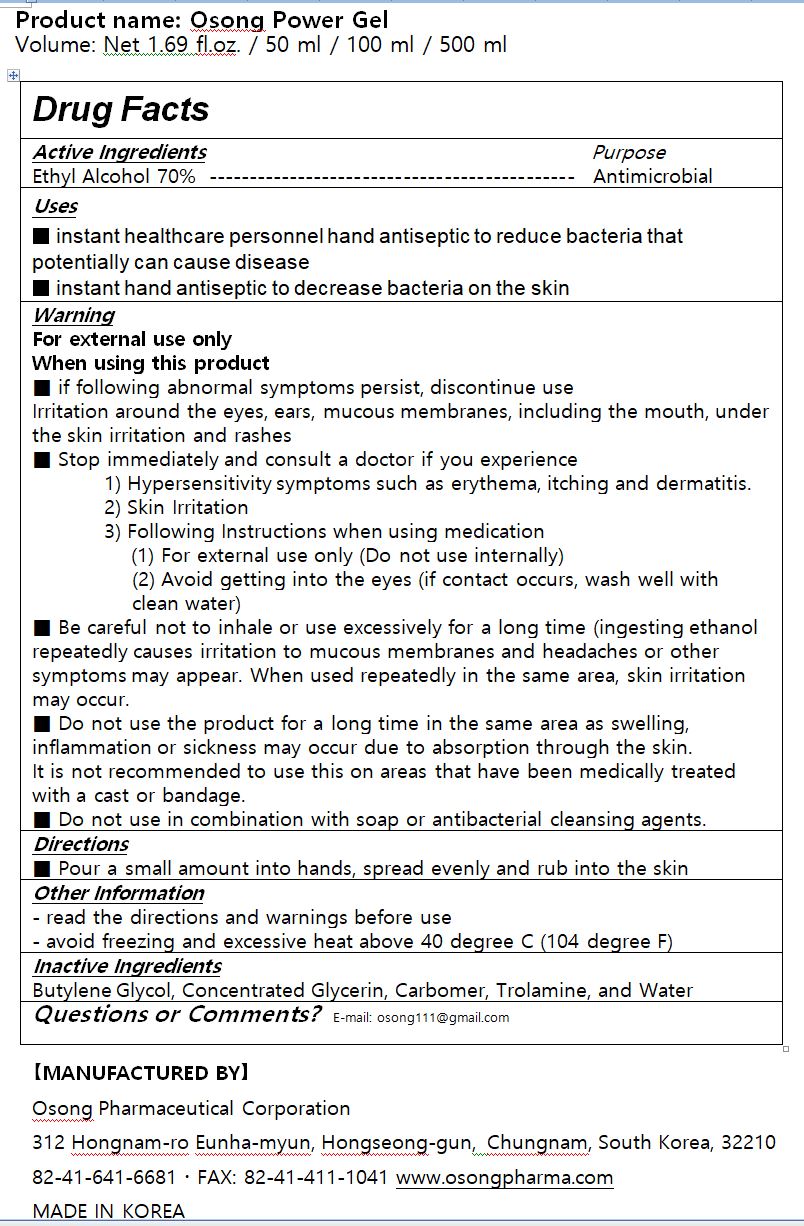 DRUG LABEL: Osong Power gel
NDC: 81294-0001 | Form: GEL
Manufacturer: Osong Co., Ltd.
Category: otc | Type: HUMAN OTC DRUG LABEL
Date: 20201225

ACTIVE INGREDIENTS: ALCOHOL 70 mL/100 mL
INACTIVE INGREDIENTS: BUTYLENE GLYCOL; WATER; CARBOMER 940; TROLAMINE

Drug Facts

ACTIVE INGREDIENT

alcohol

PURPOSE

■ instant healthcare personnel hand antiseptic to reduce bacteria that potentially can cause disease

■ instant hand antiseptic to decrease bacteria on the skin

KEEP OUT OF REACH OF THE CHILDREN

INDICATIONS AND USAGE

■ Pour a small amount into hands, spread evenly and rub into the skin

WARNINGS

For external use only

When using this product

■ if following abnormal symptoms persist, discontinue use

Irritation around the eyes, ears, mucous membranes, including the mouth, under the skin irritation and rashes

■ Stop immediately and consult a doctor if you experience

1) Hypersensitivity symptoms such as erythema, itching and dermatitis.

2) Skin Irritation

3) Following Instructions when using medication

(1) For external use only (Do not use internally)

(2) Avoid getting into the eyes (if contact occurs, wash well with clean water)

■ Be careful not to inhale or use excessively for a long time (ingesting ethanol repeatedly causes irritation to mucous membranes and headaches or other symptoms may appear. When used repeatedly in the same area, skin irritation may occur.

■ Do not use the product for a long time in the same area as swelling, inflammation or sickness may occur due to absorption through the skin.

It is not recommended to use this on areas that have been medically treated with a cast or bandage.

■ Do not use in combination with soap or antibacterial cleansing agents.

DOSAGE AND ADMINISTRATION

for external use only

INACTIVE INGREDIENT

Butylene Glycol, Concentrated Glycerin, Carbomer, Trolamine, and Water